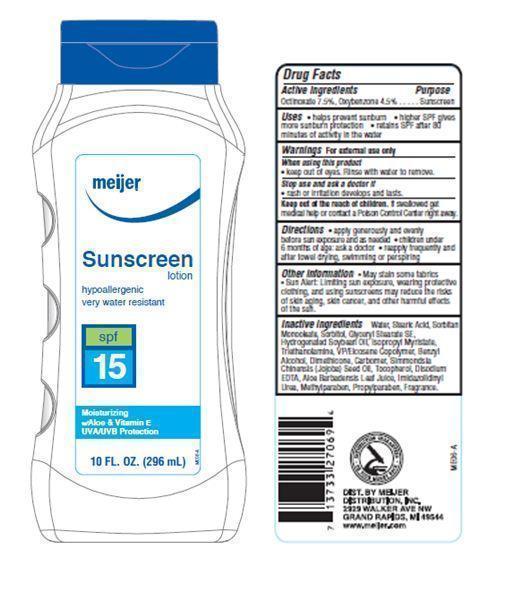 DRUG LABEL: Meijer Sunscreen SPF 15
                
NDC: 41250-025 | Form: LOTION
Manufacturer: Meijer Distribution Inc
Category: otc | Type: HUMAN OTC DRUG LABEL
Date: 20130717

ACTIVE INGREDIENTS: OCTINOXATE 7.5 g/100 g; OXYBENZONE 4.5 g/100 g
INACTIVE INGREDIENTS: METHYLPARABEN; PROPYLPARABEN; WATER; STEARIC ACID; SORBITAN MONOSTEARATE; SORBITOL; GLYCERYL STEARATE SE; HYDROGENATED SOYBEAN OIL; ISOPROPYL MYRISTATE; TROLAMINE; BENZYL ALCOHOL; DIMETHICONE; JOJOBA OIL; TOCOPHEROL; EDETATE DISODIUM; ALOE VERA LEAF; IMIDUREA

Drug Facts

Active ingredients

Octinoxate 7.5%

Oxybenzone 4.5%

Uses

- helps prevent suburn
- higher SPF gives more sunburn protection
- retains SPF after 80 minutes of activity in water

Warnings

For external use only

When using this product

- keep out of eyes. Rinse with water to remove

Stop use and ask a doctor if

- rash or irritation develops and lasts

KEEP OUT OF REACH OF CHILDREN

Keep out of the reach of children. If swallowed get medical help or contact a Poison Control Center right away.

Directions

- apply generously and evenly before sun exposure and as needed
- children under 6 months of age: ask a doctor
- reapply frequently and after towel drying, swimming or perspiring

Other information

- may stain some fabrics
- Sun Alert: Limiting sun exposure, wearing protective clothing, and using sunscreens may reduce the risks of skin aging, skin cancer and other harmful effects of the sun

Inactive ingredients

Water, Stearic Acid, Sorbitan Oleate, Sorbitol, Glyceryl Stearate SE, Hydrogenated Soybean Oil, Isopropyl Myristate, Triethanolamine, VP/Eicosene Copolymer, Benzyl Alcohol, Dimethicone, Carbomer, Simmondsia Chinensis (Jojoba) Seed Oil, Tocopherol, Disodium EDTA, Aloe Barbadensis Leaf Juice, Imidazolidinyl Urea, Methylparaben, Propylparaben, Fragrance.

Principal Display Panel

meijer

Sunscreen lotion

hypoallergenic

very water resistant

spf 15

Moisturizing

w/Aloe and Vitamin E

UVA/UVB Protection

10 FL. OZ. (296 mL)

Purpose

Sunscreen